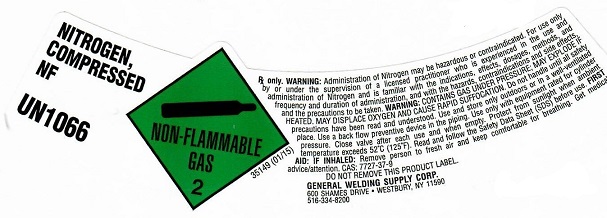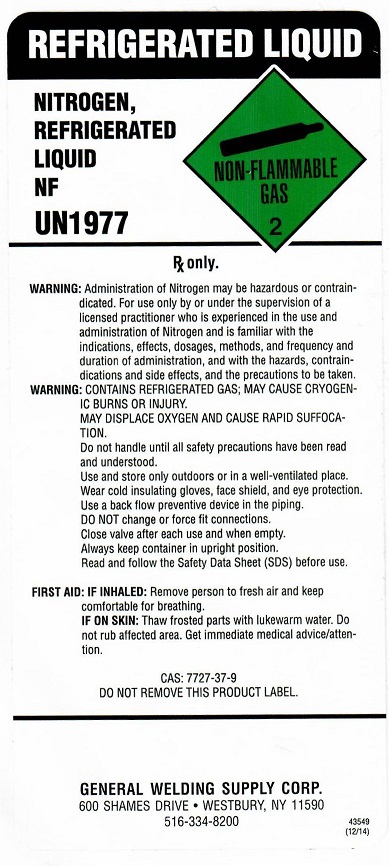 DRUG LABEL: nitrogen
NDC: 20703-001 | Form: GAS
Manufacturer: General Welding Supply Corp.
Category: prescription | Type: HUMAN PRESCRIPTION DRUG LABEL
Date: 20251227

ACTIVE INGREDIENTS: NITROGEN 999 mL/1 L

Nitrogen Label

PACKAGE LABEL

NITROGEN, COMPRESSED NF UN 1066 NON-FLAMMABLE GAS 2
Rx only. WARNING: Administration of Nitrogen may be hazardous or contraindicated. For use only by or under the supervision of a licensed practitioner who is experienced in the use and administration of Nitrogen and is familiar with the indications, effects, dosages, methods, and frequency and duration of administration, and with the hazards, contraindications, and side effects and the precautions to be taken. WARNING: CONTAINS GAS UNDER PRESSURE; MAY EXPLODE IF HEATED. MAY DISPLACE OXYGEN AND CAUSE RAPID SUFFOCATION. Do not handle until all safety precautions have been read and understood. Use and store only outdoors or in a well-ventilated place. Use a back flow preventive device in the piping. Use only with equipment rated for cylinder pressure. Close valve after each use and when empty. Protect from sunlight when ambient temperature exceeds 52 degrees C (125 degrees F). Read and follow the Safety Data Sheet (SDS) before use. FIRST AID: IF INHALED: Remove person to fresh air and keep comfortable for breathing. Get medical advice/attention.
CAS: 7727-37-9 DO NOT REMOVE THIS PRODUCT LABEL.
GENERAL WELDING SUPPLY CORP. 600 SHAMES DRIVE . WESTBURY, NY 11590 516-334-8200

PACKAGE LABEL

NITROGEN, REFRIGERATED LIQUID NF UN1977 NON-FLAMMABLE GAS 2
WARNING: Rx ONLY. Administration of Nitrogen may be hazardous or contraindicated. For use only by or under the supervision of a licensed practitioner who is experienced in the use and administration of Nitrogen and is familiar with the indications, effects, dosages, methods, and frequency and duration of administration, and with the hazards, contraindications, and side effects and the precautions to be taken. WARNING: CONTAINS GAS UNDER PRESSURE; MAY EXPLODE IF HEATED. MAY DISPLACE OXYGEN AND CAUSE RAPID SUFFOCATION. Do not handle until all safety precautions have been read and understood. Use and store only outdoors or in a well-ventilated place. Wear cold insulating gloves, face shield, and eye protection. Use a back flow preventive device in the piping. DO NOT change or force fit connections. Close valve after each use and when empty. Always keep container in upright position. Read and follow the Safety Data Sheet (SDS) before use. FIRST AID: IF INHALED: Remove person to fresh air and keep comfortable for breathing. IF ON SKIN: Thaw frosted parts with lukewarm water. Do not rub affected area. Get immediate medical advice/attention. CAS: 7727-37-9
DO NOT REMOVE THIS PRODUCT LABEL
GENERAL WELDING SUPPLY CORP. 600 SHAMES DRIVE . WESTBURY, NY 11590 516-334-8200